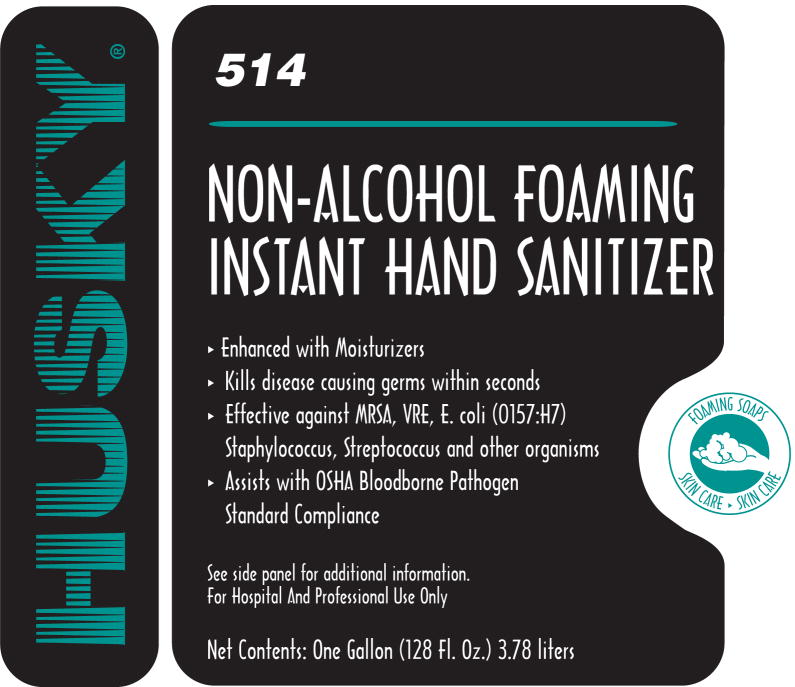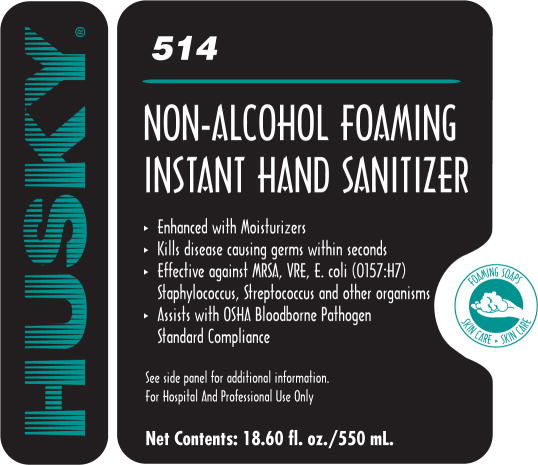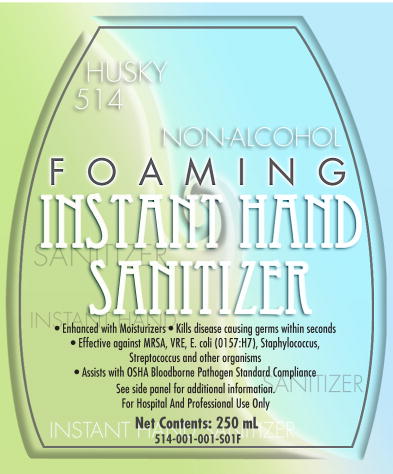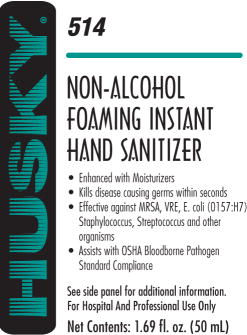 DRUG LABEL: HUSKY 514 Non-Alcohol Foaming Instant Hand Sanitizer
NDC: 63779-514 | Form: SOLUTION
Manufacturer: Canberra Corporation
Category: otc | Type: HUMAN OTC DRUG LABEL
Date: 20091103

ACTIVE INGREDIENTS: benzalkonium chloride 1 g/1000 mL
INACTIVE INGREDIENTS: water; dihydroxypropyl peg-5 linoleammonium chloride; glycereth-2 cocoate; behentrimonium chloride; dihydroxyethyl cocamine oxide

Husky® 514
NON-ALCOHOL FOAMING INSTANT HAND SANITIZER

Active Ingredient

Benzalkonium Chloride 0.1%

Purpose

Antimicrobial

Uses

- For hand sanitizing to decrease bacteria on the skin
- Recommended for repeated use

Warning

For external use only

When using this product avoid contact with eyes. In case of eye contact, flush with water.

Stop use and ask a doctor if irritation or redness develops, or if condition persists for more than 72 hours.

Keep out of reach of children. If swallowed, get medical help or contact a Poison Control Center right away.

Directions

- Pump a small amount of foam into palm of hand
- Rub thoroughly over all surfaces of both hands
- Rub hands together briskly until dry

Inactive Ingredients

Water, dihydroxpropyl PEG-5 linoleammonium chloride, glycereth-2, cocoate, behentrimonium chloride, dihydroxyethyl cocamine oxide, fragrance

Manufactured By:
CANBERRA CORPORATION
3610 Holland-Sylvania Rd.
Toledo, Ohio 43615

Label Content for 128 Fl. Oz:

Husky®

514

NON-ALCOHOL FOAMING INSTANT HAND SANITIZER

- Enhanced with Moisturizers
- Kills disease causing germs within seconds
- Effective against MRSA, VRE, E. coli (0157:H7), Staphylococcus, Streptococcus and other organisms
- Assists with OSHA Bloodborne Pathogen Standard Compliance

See side panel for additional information.

For Hospital And Professional Use Only

Net Contents: One gallon (128 Fl. Oz.) 3.78 liters

Label Content for 18.60 Fl. Oz:

Husky®

514

NON-ALCOHOL FOAMING INSTANT HAND SANITIZER

• Enhanced with Moisturizers

• Kills disease causing germs within seconds

• Effective against MRSA, VRE, E. coli (0157:H7), Staphylococcus, Streptococcus and other organisms

• Assists with OSHA Bloodborne Pathogen Standard Compliance

See side panel for additional information.

For Hospital And Professional Use Only

Net Contents: 18.60 fl. oz./550 mL.

Label Content for 250 mL:

Husky

514

NON-ALCOHOL FOAMING INSTANT HAND SANITIZER

• Enhanced with Moisturizers

• Kills disease causing germs within seconds

• Effective against MRSA, VRE, E. coli (0157:H7), Staphylococcus, Streptococcus and other organisms

• Assists with OSHA Bloodborne Pathogen Standard Compliance

See side panel for additional information.

For Hospital And Professional Use Only

Net Contents: 250 mL

514-001-001-S01F

Label Content for 1.69 Fl Oz:

Husky

514

NON-ALCOHOL FOAMING INSTANT HAND SANITIZER

• Enhanced with Moisturizers

• Kills disease causing germs within seconds

• Effective against MRSA, VRE, E. coli (0157:H7), Staphylococcus, Streptococcus and other organisms

• Assists with OSHA Bloodborne Pathogen Standard Compliance

See side panel for additional information.

For Hospital And Professional Use Only

Net Contents: 1.69 fl. Oz (50 mL)